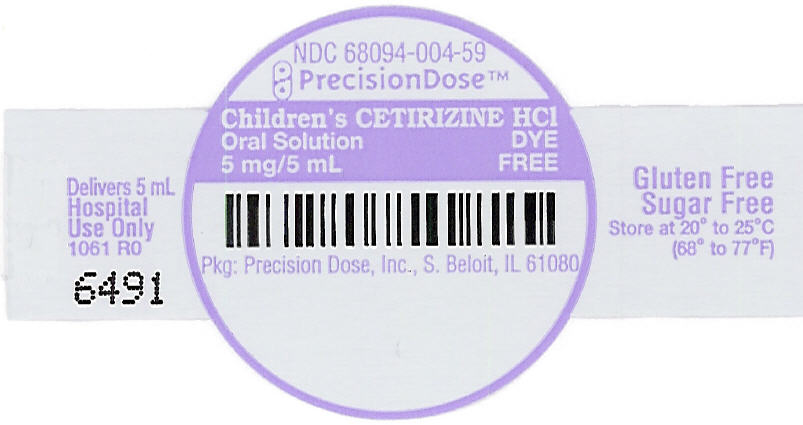 DRUG LABEL: Dye Free Childrens Cetirizine Hydrocholride
NDC: 68094-004 | Form: SOLUTION
Manufacturer: Precision Dose, Inc.
Category: otc | Type: HUMAN OTC DRUG LABEL
Date: 20250212

ACTIVE INGREDIENTS: Cetirizine Hydrochloride 5 mg/5 mL
INACTIVE INGREDIENTS: anhydrous citric acid; propylene glycol; water; sodium benzoate; sorbitol; sucralose

Dye Free Children's Cetirizine Hydrochloride
Oral Solution

5 mg/5 mL Grape Flavor

For Hospital Use Only

LI1660 Rev.10/24

Drug Facts

Active ingredient (in each 5 mL)

Cetirizine HCl 5 mg

Purpose

Antihistamine

Uses

temporarily relieves these symptoms due to hay fever or other upper respiratory allergies:

- runny nose
- sneezing
- itchy, watery eyes
- itching of the nose or throat

Warnings

Do not use if you have ever had an allergic reaction to this product or any of its ingredients or to an antihistamine containing hydroxyzine.

Ask a doctor before use if you have liver or kidney disease. Your doctor should determine if you need a different dose.

Ask a doctor or pharmacist before use if you are taking tranquilizers or sedatives.

When using this product

- drowsiness may occur
- avoid alcoholic drinks
- alcohol, sedatives, and tranquilizers may increase drowsiness
- be careful when driving a motor vehicle or operating machinery

Stop use and ask a doctor if an allergic reaction to this product occurs. Seek medical help right away.

If pregnant or breast-feeding:

- if breast-feeding: not recommended
- if pregnant: ask a health professional before use.

Keep out of reach of children. In case of overdose, get medical help or contact a Poison Control Center right away. (1-800-222-1222)

Directions

- Use as directed per healthcare professional.
- mL = milliliter

adults and children 6 years and over | 5 mL or 10 mL once daily depending upon severity of symptoms; do not take more than 10 mL in 24 hours.
adults 65 years and over | 5 mL once daily; do not take more than 5 mL in 24 hours.
children 2 to under 6 years of age | 2.5 mL once daily. If needed, dose can be increased to a maximum of 5 mL once daily or 2.5 mL every 12 hours. Do not give more than 5 mL in 24 hours.
children under 2 years of age | ask a doctor
consumers with liver or kidney disease | ask a doctor

Other Information

- store between 20° to 25°C (68° to 77°F)

Inactive ingredients

anhydrous citric acid, artificial grape flavor, propylene glycol, purified water, sodium benzoate, sorbitol solution, sucralose

Dye Free, Gluten Free, Sugar Free

How Supplied

NDC 68094-004-62
5 mL per unit dose cup
Thirty (30) cups per shipper

Packaged By:
Precision Dose, Inc.
South Beloit, IL 61080

For inquiries call Precision Dose, Inc. at 1-800-397-9228 or email druginfo@precisiondose.com.

LI1660 Rev.10/24

PRINCIPAL DISPLAY PANEL - 5 mL Cup Label

NDC 68094-004-59
PrecisionDose ™

Children's CETIRIZINE HCl
Oral Solution
5 mg/5 mL
DYE
FREE

Pkg: Precision Dose, Inc., S. Beloit, IL 61080